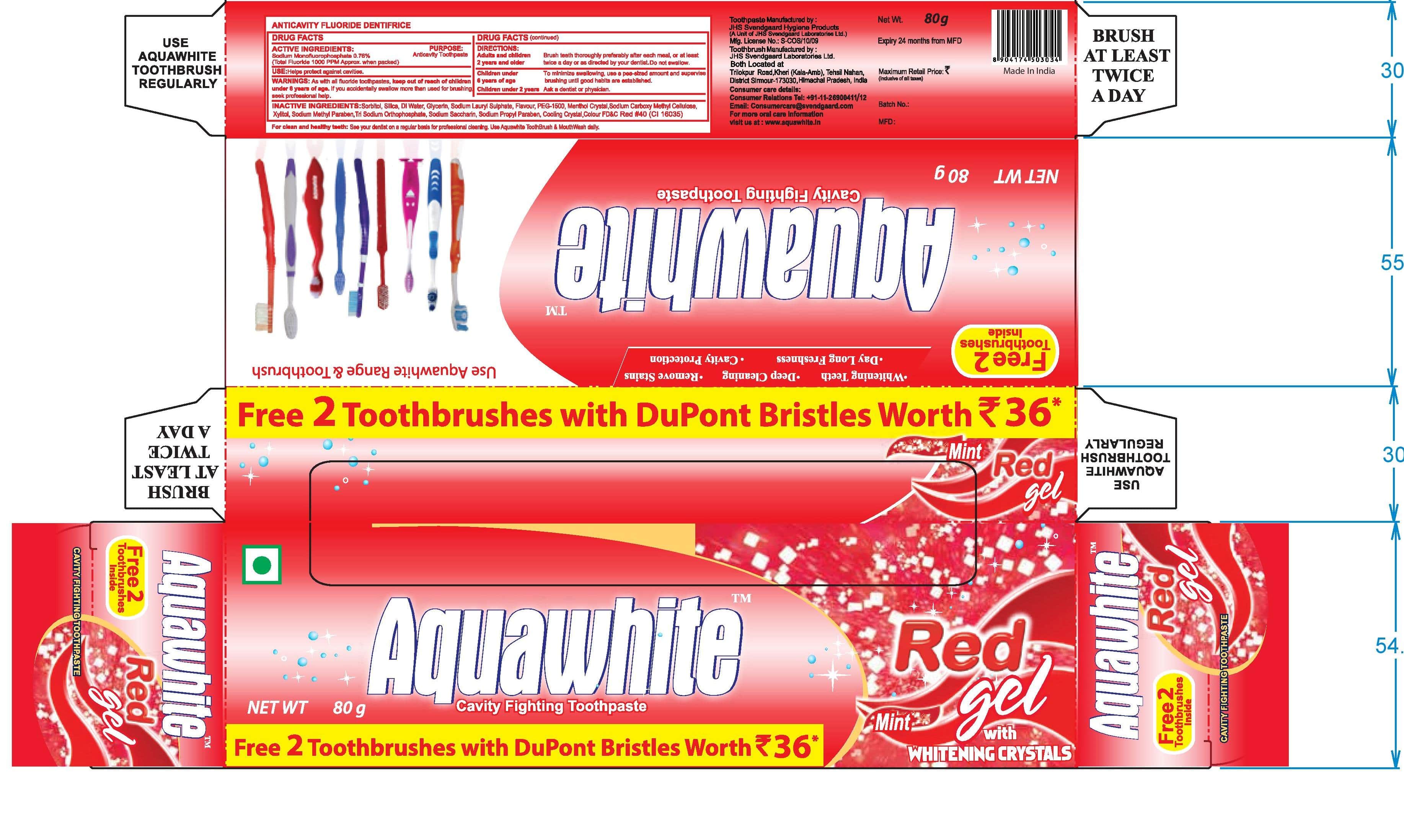 DRUG LABEL: AquaWhite Red Gel Cavity FightingTooth
NDC: 72025-003 | Form: PASTE, DENTIFRICE
Manufacturer: JHS SVENDGAARD LABORATORIES LIMITED
Category: otc | Type: HUMAN OTC DRUG LABEL
Date: 20180116

ACTIVE INGREDIENTS: SODIUM MONOFLUOROPHOSPHATE 0.1 g/100 g
INACTIVE INGREDIENTS: WATER; SORBITOL; SODIUM LAURYL SULFATE; CARBOXYMETHYLCELLULOSE SODIUM; GLYCERIN; XANTHAN GUM; MENTHOL; SACCHARIN SODIUM; XYLITOL; SODIUM PHOSPHATE; FD&C RED NO. 40

Active Ingredient

Sodium Monofluorophosphate 0.76%

Purpose:

Anticavity

Uses:

Helps protect against cavities

Warnings:

If you accidentally swallow more than used for brushing, seek professional help

Keep out of reach of children under 6 years of age

Directions:

- Adults and children 2 years and older:
- Brush teeth thoroughly after meals or at least twice a day or use as directed by a dentist.
- Do not swallow
- Children under 6 Years of Age

- To minimize swallowing use a pea-sized amount and supervise children's brushing untill good habits are established.

Children under 2 years of age:

- Ask a dentist or physician

Inactive Ingredients:

Sorbitor, Water, Silica, Glycerin, Sodium Lauryl Suphate, Flavor, PEG-1500, Sodium Carboxymethylcellulose, Xylitol, Xanthan Gum, Sodium Methyl Paraben, Sodium Phosphate, Sodium Propyl Paraben, Sodium Saccharin, Cooling Crystal, FD&C Red 40